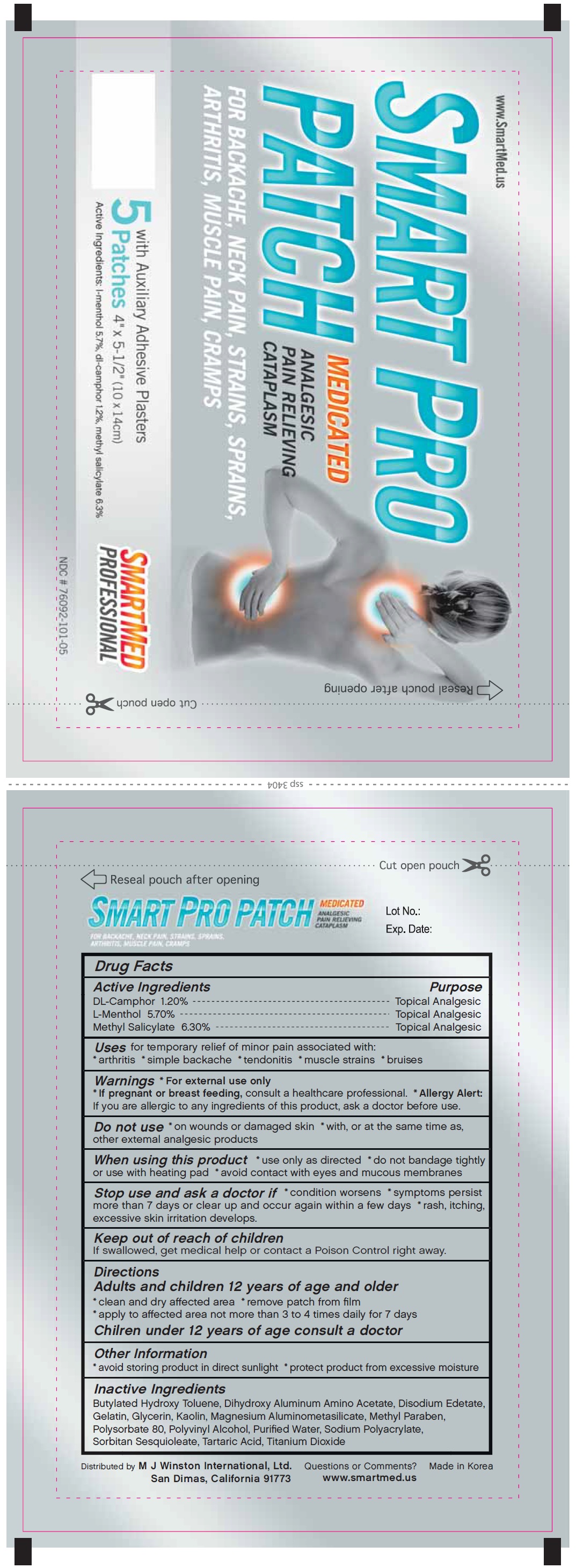 DRUG LABEL: SMART PRO
NDC: 76092-101 | Form: PATCH
Manufacturer: M J Winston International Ltd..
Category: otc | Type: HUMAN OTC DRUG LABEL
Date: 20110620

ACTIVE INGREDIENTS: CAMPHOR (SYNTHETIC) 1.2 mg/1 1; MENTHOL 5.7 mg/1 1; METHYL SALICYLATE 6.3 mg/1 1
INACTIVE INGREDIENTS: BUTYLATED HYDROXYTOLUENE; DIHYDROXYALUMINUM AMINOACETATE; EDETATE DISODIUM; GELATIN; GLYCERIN; KAOLIN; ALMASILATE; METHYLPARABEN; POLYSORBATE 80; POLYVINYL ALCOHOL; WATER; SODIUM POLYACRYLATE (8000 MW); SORBITAN SESQUIOLEATE; TARTARIC ACID; TITANIUM DIOXIDE

Drug Facts

Active ingredient

- DL-Camphor 1.20 %
- L-Menthol 5.70 %
- Methyl Salicylate 6.30 %

Purpose

Topical Analgesic

Uses

for temporary relief of minor pain associated with:

- arthritis
- simple backache
- tendonitis
- muscle strains
- bruises

Warnings

- For external use only
- If pregnant or breast feeding, consult a healthcare professional.
- Allergy Alert: If you are allergic to any ingredients of this product, ask a doctor before use.

When using this product

- use only as directed
- do not bandage tightly or use with heating pad
- avoid contact with eyes and mucous membranes

Stop use and ask a doctor if

- condition worsens
- symptoms persist more than 7 days or clear up and occur again within a few days
- rash, itching, excessive skin irritation develops.

Keep out of reach of children.

If swallowed, get medical help or contact a Poison Control Center right away.

Directions

- Adults and children 12 years of age and older
- clean and dry affected
- remove patch from film
- apply to affected area not more than 3 to 4 times daily for 7 days
- Children under 12 years of age consult a doctor

Other information

- avoid storing product in direct sunlight
- protect product from excessive moisture.

Inactive ingredients

Butylated Hydroxy Toluene, Dihydroxy Aluminum Amino Acetate, Disodium Edetate, Gelatin, Glycerin, Kaolin, Magenesium Aluminometasilicate, Methyl Paraben, Polysorbate 80, Polyvinyl Alcohol, Purified Water, Sodium Polyacrylate, Sorbitan Sesquioleate, Tartaric Acid, Titanium Dioxide

Questions or Comments?

Distributed by

M J Winston International, Ltd.

San Dimas, California 91773

www.smartmed.us

Made in Korea

Package/Label Principal Display Panel

SMART PRO PATCH